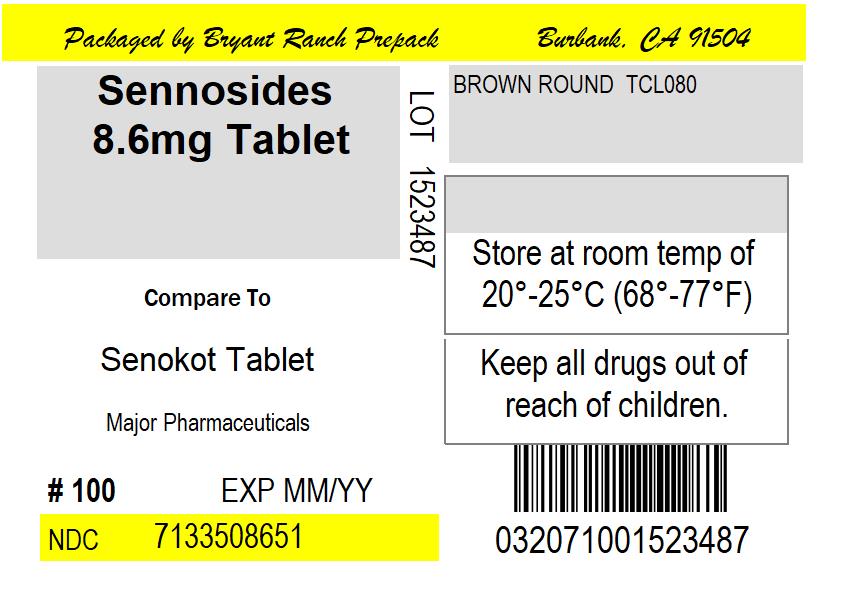 DRUG LABEL: SENNA TIME
NDC: 71335-0865 | Form: TABLET, COATED
Manufacturer: Bryant Ranch Prepack
Category: otc | Type: HUMAN OTC DRUG LABEL
Date: 20220510

ACTIVE INGREDIENTS: SENNOSIDES A AND B 8.6 mg/1 1
INACTIVE INGREDIENTS: CROSCARMELLOSE SODIUM; DIBASIC CALCIUM PHOSPHATE DIHYDRATE; HYPROMELLOSE, UNSPECIFIED; MAGNESIUM STEARATE; MICROCRYSTALLINE CELLULOSE; MINERAL OIL

DRUG FACTS

Active ingredient (in each tablet)
Sennosides 8.6 mg

Keep out of reach of children. In case of overdose, get medical help or contact a Poison Control Center right away

Purpose
Laxative

Uses

- relieves occasional constipation (irregularity)
- generally causes bowel movement in 6-12 hours

DOSAGE AND ADMINISTRATION

Directions: Take preferably at bedtime or as directed by a doctor; if you do not have a comfortable bowel movement by the second day, increase dose by one tablet (do not exceed maximum dosage) or decrease dose until you are comfortable.Adults and children 12 years and over - starting dosage: 2 tablets once a day Maximum dosage: 4 tablets twice a dayChildren 6 to under 12 years - starting dosage: 1 tablet once a day Maximum dosage: 2 tablets twice a dayChildren 2 to under 6 years - starting dosage: 1/2 tablet once a day Maximum dosage: 1 tablet twice a dayChildren under 2 years - ask a doctor

WARNINGS

WARNINGS: Do not use laxative products for longer than 1 week unless directed by a doctor

Ask a doctor before use if you have

- stomach pain
- nausea
- vomiting
- noticed a sudden change in bowel movements that continues over a period of 2 weeks

INACTIVE INGREDIENT

Inactive Ingredients: croscarmellose sodium, dibasic calcium phosphate dihydrate, hypromellose, magnesium stearate, microcrystalline cellulose, mineral oil

HOW SUPPLIED

NDC: 71335-0865-1 100 TABLET in a BOTTLE

NDC: 71335-0865-2 60 TABLET in a BOTTLE

NDC: 71335-0865-3 120 TABLET in a BOTTLE

NDC: 71335-0865-4 56 TABLET in a BOTTLE

NDC: 71335-0865-5 30 TABLET in a BOTTLE

NDC: 71335-0865-6 90 TABLET in a BOTTLE